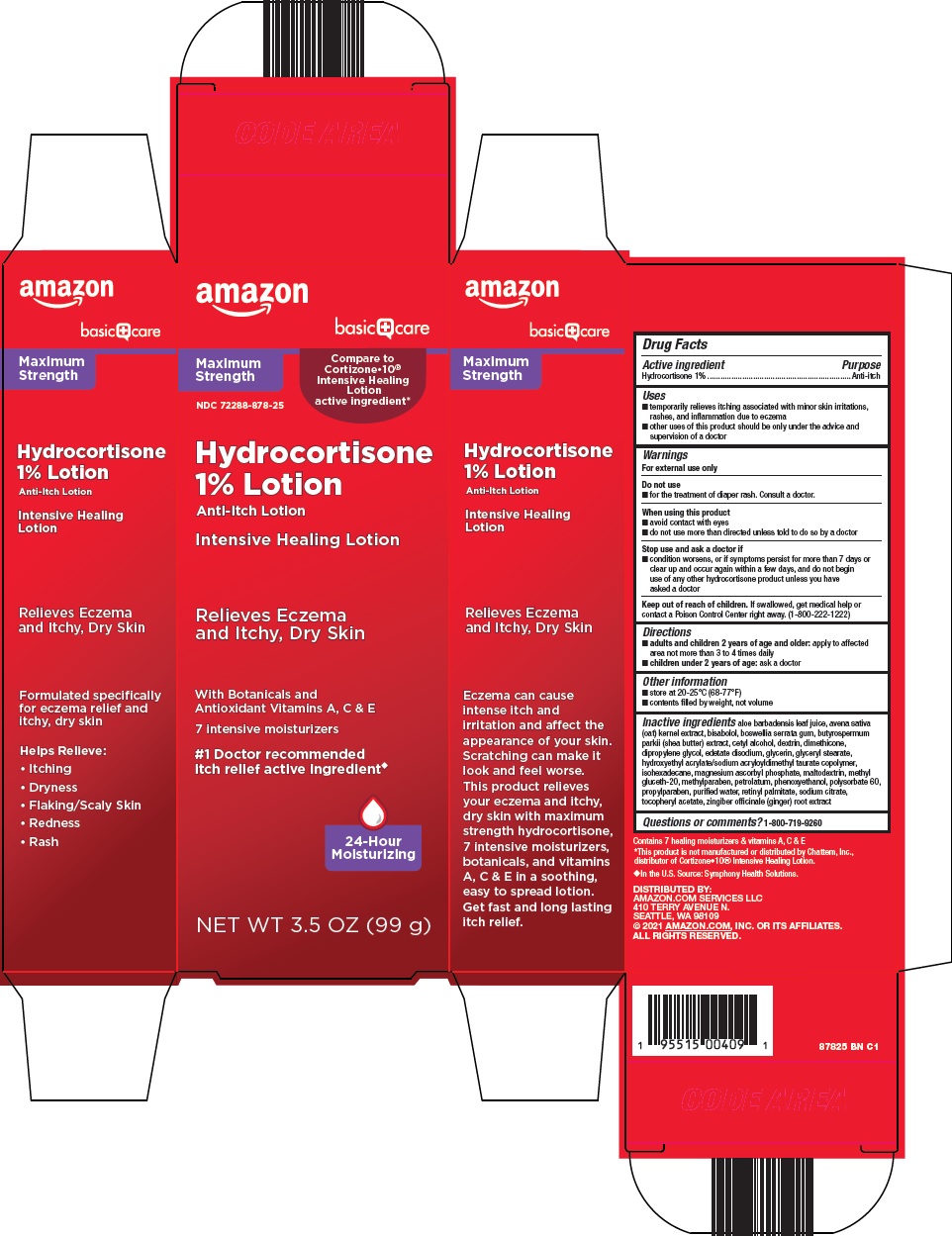 DRUG LABEL: basic care hydrocortisone
NDC: 72288-878 | Form: LOTION
Manufacturer: Amazon.com Services LLC
Category: otc | Type: HUMAN OTC DRUG LABEL
Date: 20241031

ACTIVE INGREDIENTS: HYDROCORTISONE 1 g/100 g
INACTIVE INGREDIENTS: ALOE VERA LEAF; OAT; LEVOMENOL; INDIAN FRANKINCENSE; CETYL ALCOHOL; ICODEXTRIN; DIMETHICONE; DIPROPYLENE GLYCOL; EDETATE DISODIUM; GLYCERIN; GLYCERYL MONOSTEARATE; ISOHEXADECANE; MAGNESIUM ASCORBYL PHOSPHATE; MALTODEXTRIN; METHYL GLUCETH-20; METHYLPARABEN; PETROLATUM; PHENOXYETHANOL; POLYSORBATE 60; PROPYLPARABEN; WATER; VITAMIN A PALMITATE; SODIUM CITRATE, UNSPECIFIED FORM; GINGER; .ALPHA.-TOCOPHEROL ACETATE

Amazon Hydrocortisone 1% Lotion Drug Facts

Active ingredient

Hydrocortisone 1%

Purpose

Anti-itch

Uses

- temporarily relieves itching associated with minor skin irritations, rashes, and inflammation due to eczema
- other uses of this product should be only under the advice and supervision of a doctor

Warnings

For external use only

Do not use

for the treatment of diaper rash. Consult a doctor.

When using this product

- avoid contact with eyes
- do not use more than directed unless told to do so by a doctor

Stop use and ask a doctor if

- condition worsens, or if symptoms persist for more than 7 days or clear up and occur again within a few days, and do not begin use of any other hydrocortisone product unless you have asked a doctor

Keep out of reach of children.

If swallowed, get medical help or contact a Poison Control Center right away. (1-800-222-1222)

Directions

- adults and children 2 years of age and older: apply to affected area not more than 3 to 4 times daily
- children under 2 years of age: ask a doctor

Other information

- store at 20-25°C (68-77°F)
- contents filled by weight, not volume

Inactive ingredients

aloe barbadensis leaf juice, avena sativa (oat) kernel extract, bisabolol, boswellia serrata gum, butyrospermum parkii (shea butter) extract, cetyl alcohol, dextrin, dimethicone, dipropylene glycol, edetate disodium, glycerin, glyceryl stearate, hydroxyethyl acrylate/sodium acryloyldimethyl taurate copolymer, isohexadecane, magnesium ascorbyl phosphate, maltodextrin, methyl gluceth-20, methylparaben, petrolatum, phenoxyethanol, polysorbate 60, propylparaben, purified water, retinyl palmitate, sodium citrate, tocopheryl acetate, zingiber officinale (ginger) root extract

Questions or comments?

1-800-719-9260

Package/Label Principal Display Panel

Maximum Strength

Compare to Cortizone • 10® Intensive Healing Lotion

active ingredient

Hydrocortisone 1% Lotion

Anti-Itch Lotion

Intensive Healing Lotion

Relieves Eczema and Itchy, Dry Skin

With Botanicals and Antioxidant Vitamins A, C & E

7 intensive moisturizers

#1 Doctor recommended itch relief active ingredient

24-Hour Moisturizing

NET WT 3.5 OZ (99 g)